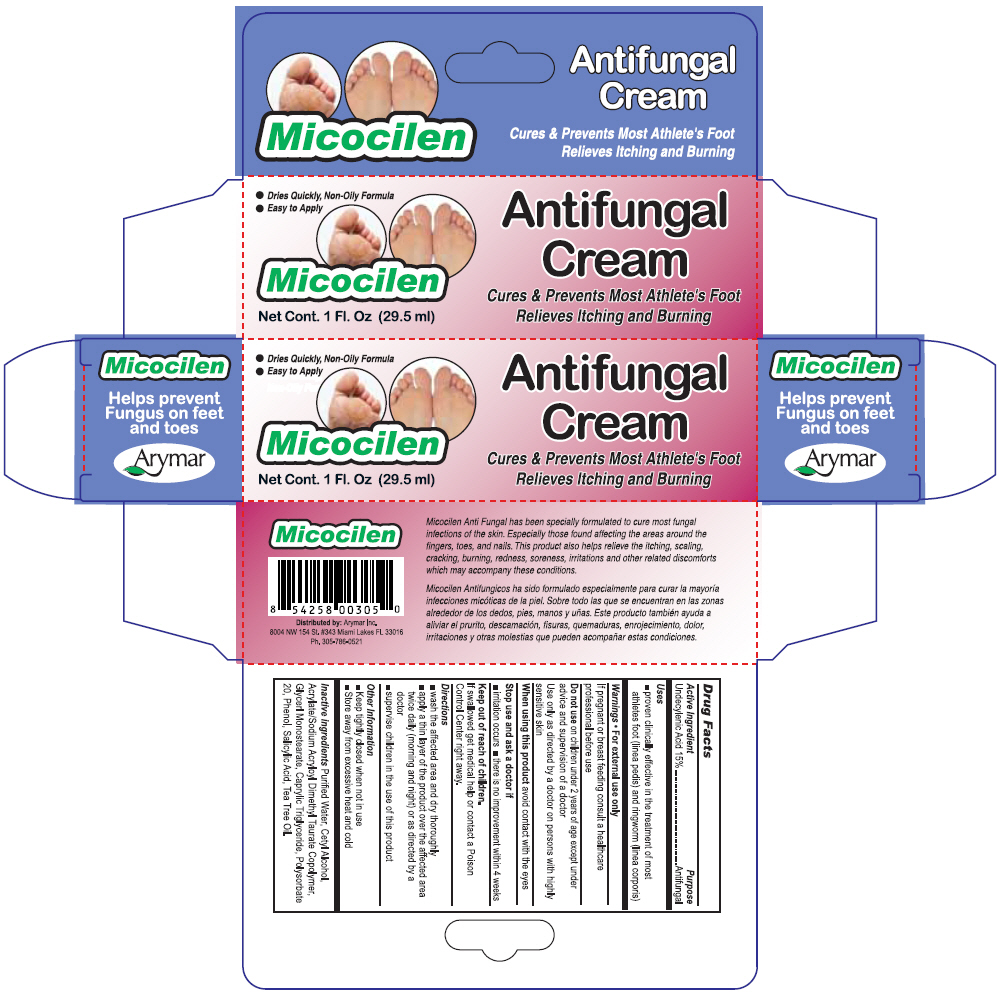 DRUG LABEL: Micocilen
NDC: 70570-0198 | Form: CREAM
Manufacturer: Arymar Inc.
Category: otc | Type: HUMAN OTC DRUG LABEL
Date: 20190304

ACTIVE INGREDIENTS: Undecylenic Acid 150 mg/1 mL
INACTIVE INGREDIENTS: Water; Cetyl Alcohol; Glyceryl Monostearate; Tricaprylin; Polysorbate 20; Phenol; Salicylic Acid; Tea Tree Oil

Micocilen

Drug Facts

Active Ingredient

Undecylenic Acid 15%

Purpose

Antifungal

Uses

- proven clinically effective in the treatment of most athletes foot (linea pedis) and ringworm (linea corporis)

Warnings

- For external use only

PREGNANCY OR BREAST FEEDING

If pregnant or breast feeding consult a healthcare professional before use

Do not use on children under 2 years of age except under advice and supervision of a doctor

Use only as directed by a doctor on persons with highly sensitive skin

When using this product avoid contact with the eyes

Stop use and ask a doctor if

- irritation occurs
- there is no improvement within 4 weeks

Keep out of reach of children. If swallowed get medical help or contact a Poison Control Center right away.

Directions

- wash the affected area and dry thoroughly
- apply a thin layer of the product over the affected area twice daily (morning and night) or as directed by a doctor
- supervise children in the use of this product

Other Information

- Keep tightly closed when not in use
- Store away from excessive heat and cold

Inactive ingredients

Purified Water, Cetyl Alcohol, Acrylate/Sodium Acryloyl Dimethyl Taurate Copolymer, Glycerl Monostearate, Caprylic Triglyceride, Polysorbate 20, Phenol, Salicylic Acid, Tea Tree Oil.

Distributed by: Arymar Inc.
8004 NW 154 St. #343 Miami Lakes FL 33016

PRINCIPAL DISPLAY PANEL - 29.5 ml Tube Carton

- Dries Quickly, Non-Oily Formula
- Easy to Apply

Micocilen

Antifungal
Cream

Cures & Prevents Most Athlete's Foot
Relieves Itching and Burning

Net Cont. 1 Fl. Oz (29.5 ml)